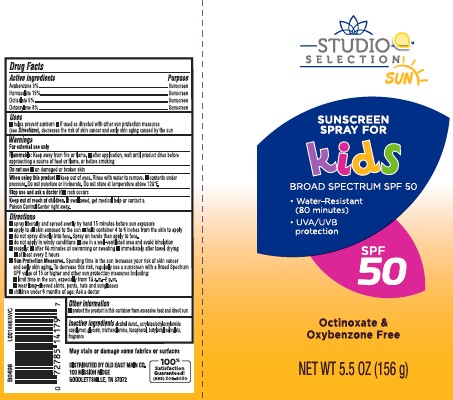 DRUG LABEL: sunscreen
NDC: 55910-874 | Form: SPRAY
Manufacturer: Old East Main Co.
Category: otc | Type: HUMAN OTC DRUG LABEL
Date: 20260302

ACTIVE INGREDIENTS: AVOBENZONE 30 mg/1 g; HOMOSALATE 150 mg/1 g; OCTISALATE 50 mg/1 g; OCTOCRYLENE 80 mg/1 g
INACTIVE INGREDIENTS: ALCOHOL; STEAROXYTRIMETHYLSILANE; GLYCERIN; TROLAMINE; TOCOPHEROL; BUTYLOCTYL SALICYLATE

Studio Selections 929.001/929AB
Sunscreen Spray for Kids

Active ingredients

Avobenzone 3%

Homosalate 15%

Octisalate 5%

Octocrylene 8%

purpose

sunscreen

uses

■ helps prevent sunburn

■ if used as directed with other sun protection measures (see Directions), decreases the risk of skin cancer and early skin aging caused by the sun

warnings

For external use only

Flammable

Keep away from fire or flame.

- after application, wait until product dries before approaching a source of heat or flame, or before smoking

do not use

- on damaged or broken skin

When using this product

- keep out of eyes. Rinse with water to remove.
- contents under pressure. Do not puncture or incinerate. Do not store at temperature above 120ºF.

stop use and ask a doctor if

- rash occurs

Keep out of reach of children.

If swallowed, get medical help or contact a Poison Conrol Center right away.

directions

■ spray liberally and spread evenly by hand 15 minutes before sun exposure
■ apply to all skin exposed to the sun
■ hold container 4 to 6 inches from the skin to apply
■ do not spray directly into face. Spray on hands then apply to face.
■ do not apply in windy conditions
■ use in a well-ventilated area and avoid inhalation
■ reapply:
■ after 80 minutes of swimming or sweating
■ immediately after towel drying
■ at least every 2 hours
■ Sun Protection Measures. Spending time in the sun increases your risk of skin cancer and early skin aging. To decrease this risk, regularly use a sunscreen with a Broad Spectrum SPF value of 15 or higher and other sun protection measures including:
■ limit time in the sun, especially from 10 a.m.–2 p.m.
■ wear long-sleeved shirts, pants, hats and sunglasses
■ children under 6 months of age: Ask a doctor

other information

- protect the product in the container from excessive heat and direct sun

inactive ingredients

alcohol denat., acrylates/octylacrylamide copolymer, glycerin, triethanolamine, tocopherol, butyloctyl salicylate, fragrance

ADVERSE REACTION

May stain or damage some fabrics of surfaces

100% Satisfaction Guaranteed!

(888) 309-9030

DISTRUBUTED BY DOLGENCORP, LLC

100 MISSION RIDGE

GOODLETTSVILLE, TN 37072

principal display panel

STUDIO SELECTION™

SUN

SUNSCREEN SPRAY FOR KIDS

BROAD SPECTRUM SPF 50

- Water-Resistant(80 minutes)
- UVA/UVB protection

SPF 50

Octinoxate, Oxybenzone & Paraben Free

NET WT 5.5 OZ (156 g)